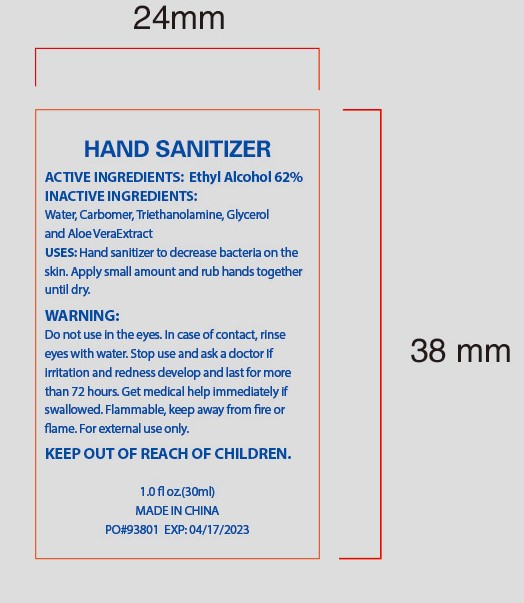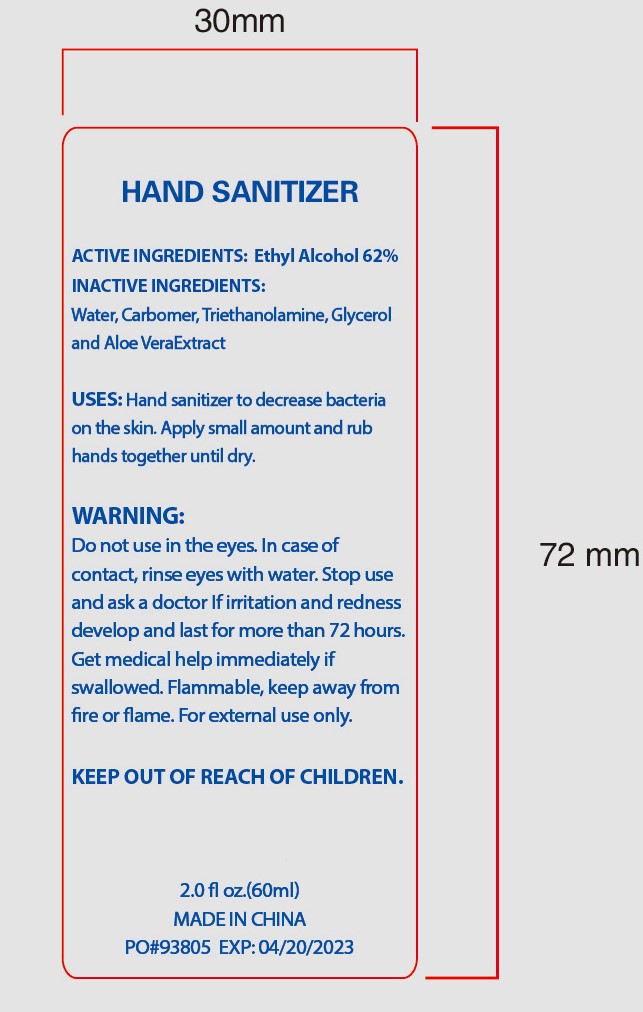 DRUG LABEL: HAND SANITIZER
NDC: 47993-227 | Form: GEL
Manufacturer: NINGBO JIANGBEI OCEAN STAR TRADING CO.,LTD
Category: otc | Type: HUMAN OTC DRUG LABEL
Date: 20201104

ACTIVE INGREDIENTS: ALCOHOL 62 g/112 mL
INACTIVE INGREDIENTS: WATER 20 g/112 mL; GLYCERIN 2 g/112 mL; CARBOMER 940 12 g/112 mL; ALOE VERA LEAF 1 g/112 mL; TRIETHANOLAMINE BENZOATE 3 g/112 mL

47993-227

Active ingredients

Ethyl Alcohol 62%

PURPOSE

Antiseptic

Warnings:

Do not use in the eyes. In case of contact，rinse eyes with water. Stop use and ask a doctor if irritation and redness develop and last for more than 72 hours. Get medical help immediately if swallowed. Flammable，keep away from fire or flame. For external use only.

Do not use in the eyes. In case of contact，rinse eyes with water.

STOP USE

if irritation and redness develop and last for more than 72 hours.

ASK DOCTOR

if irritation and redness develop and last for more than 72 hours.

Uses：

Hand sanitizer to decrease bacteria on the skin

DOSAGE AND ADMINISTRATION

Diections：

Apply small amount and rub hands together until dry.

Keep out of reach of children.

Inactive Ingredients:

Water,Carbomer,Triethanolamine,Glycerin and Aloe VeraExtract